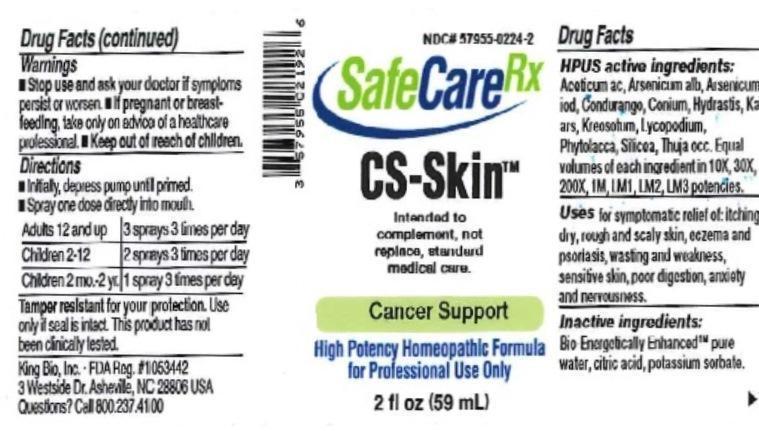 DRUG LABEL: CS Skin
NDC: 57955-0224 | Form: LIQUID
Manufacturer: King Bio Inc.
Category: homeopathic | Type: HUMAN OTC DRUG LABEL
Date: 20150625

ACTIVE INGREDIENTS: ACETIC ACID 10 [hp_X]/59 mL; ARSENIC TRIOXIDE 10 [hp_X]/59 mL; ARSENIC TRIIODIDE 10 [hp_X]/59 mL; MARSDENIA CONDURANGO BARK 10 [hp_X]/59 mL; CONIUM MACULATUM FLOWERING TOP 10 [hp_X]/59 mL; GOLDENSEAL 10 [hp_X]/59 mL; POTASSIUM ARSENITE ANHYDROUS 10 [hp_X]/59 mL; WOOD CREOSOTE 10 [hp_X]/59 mL; LYCOPODIUM CLAVATUM SPORE 10 [hp_X]/59 mL; PHYTOLACCA AMERICANA ROOT 10 [hp_X]/59 mL; SILICON DIOXIDE 10 [hp_X]/59 mL; THUJA OCCIDENTALIS LEAFY TWIG 10 [hp_X]/59 mL
INACTIVE INGREDIENTS: WATER; ANHYDROUS CITRIC ACID; POTASSIUM SORBATE

CS Skin™

ACTIVE INGREDIENT

Drug Facts__________________________________________________________________________________________________________

HPUS active ingredients: Aceticum acidum, Arsenicum album, Arsenicum iodatum, Condurango, Conium maculatum, Hydrastis canadensis, Kali arsenicosum, Kreosotum, Lycopodium clavatum, Phytolacca decandra, Silicea, Thuja occidentalis. Equal volumes of each ingredient in 10X, 30X, 200X, 1M, LM1, LM2, LM3 potencies.

INDICATIONS AND USAGE

Uses for symptomatic relief of: itching, dry, rough and scaly skin, eczema and psoriasis, wasting and weakness, sensitive skin, poor digestion, anxiety and nervousness.

Inactive Ingredients:

Bio-Energetically Enhanced™ pure water, citric acid and potassium sorbate.

Warnings

- Stop use and ask your doctor if symptoms persist or worsen.
- If pregnant or breast-feeding, take only on advice of a healthcare professional.

- Keep out of reach of children.

Directions

- Initially, depress pump until primed.
- Spray one dose directly into mouth.
- Adults 12 and up: 3 sprays 3 times per day.
- Children 2-12: 2 sprays 3 times per day.
- Children 2 mo.-2yr: 1 spray 3 times per day.

OTHER SAFETY INFORMATION

Tamper resistant for your protection. Use only if safety seal is intact. This product has not been clinically tested. Intended to complement, not replace, standard medical care.

PURPOSE

Uses for symptomatic relief of:

- itching
- dry
- rough and scaly skin
- eczema and psoriasis
- wasting and weakness
- sensitive skin
- poor digestion
- anxiety
- nervousness